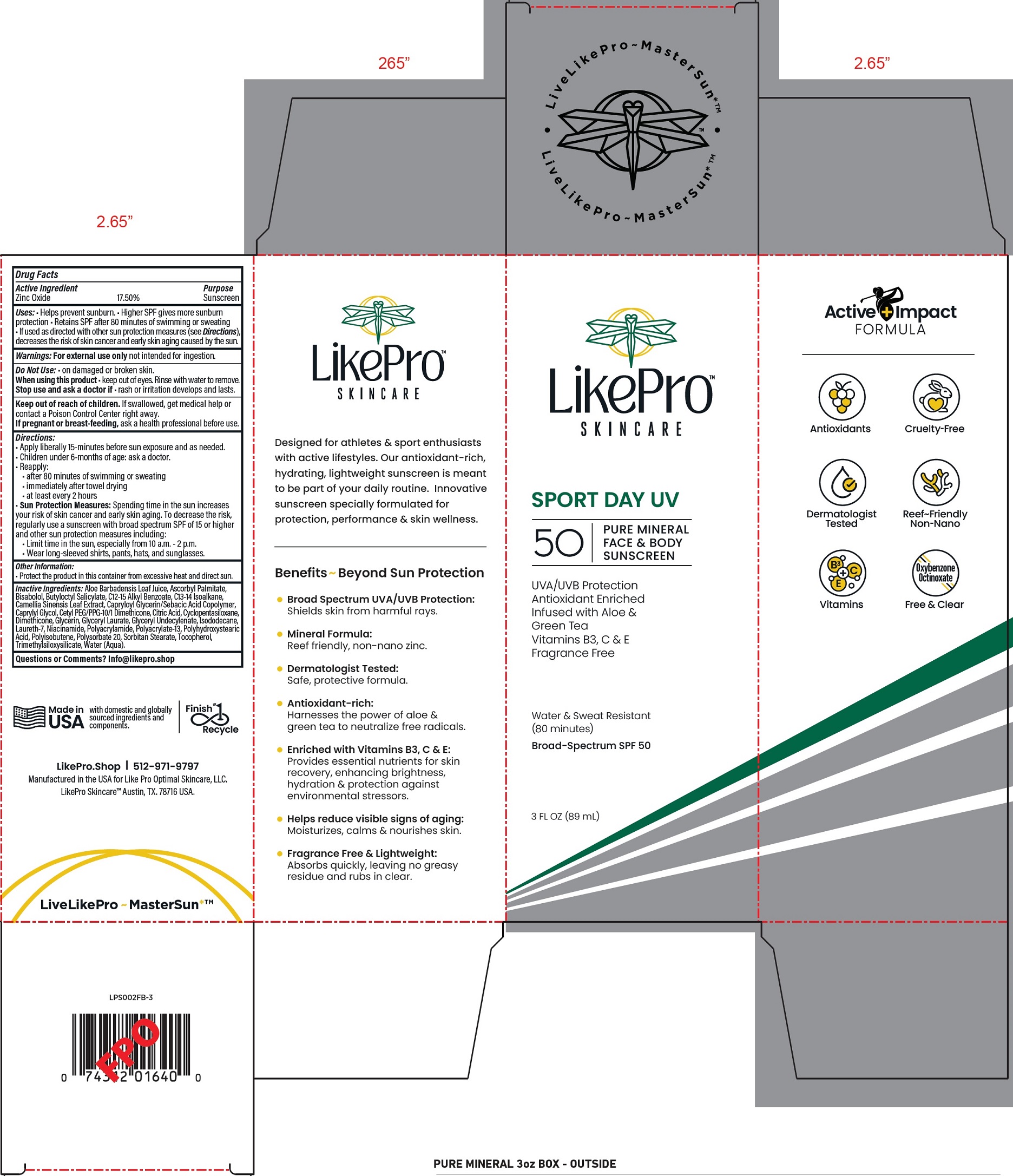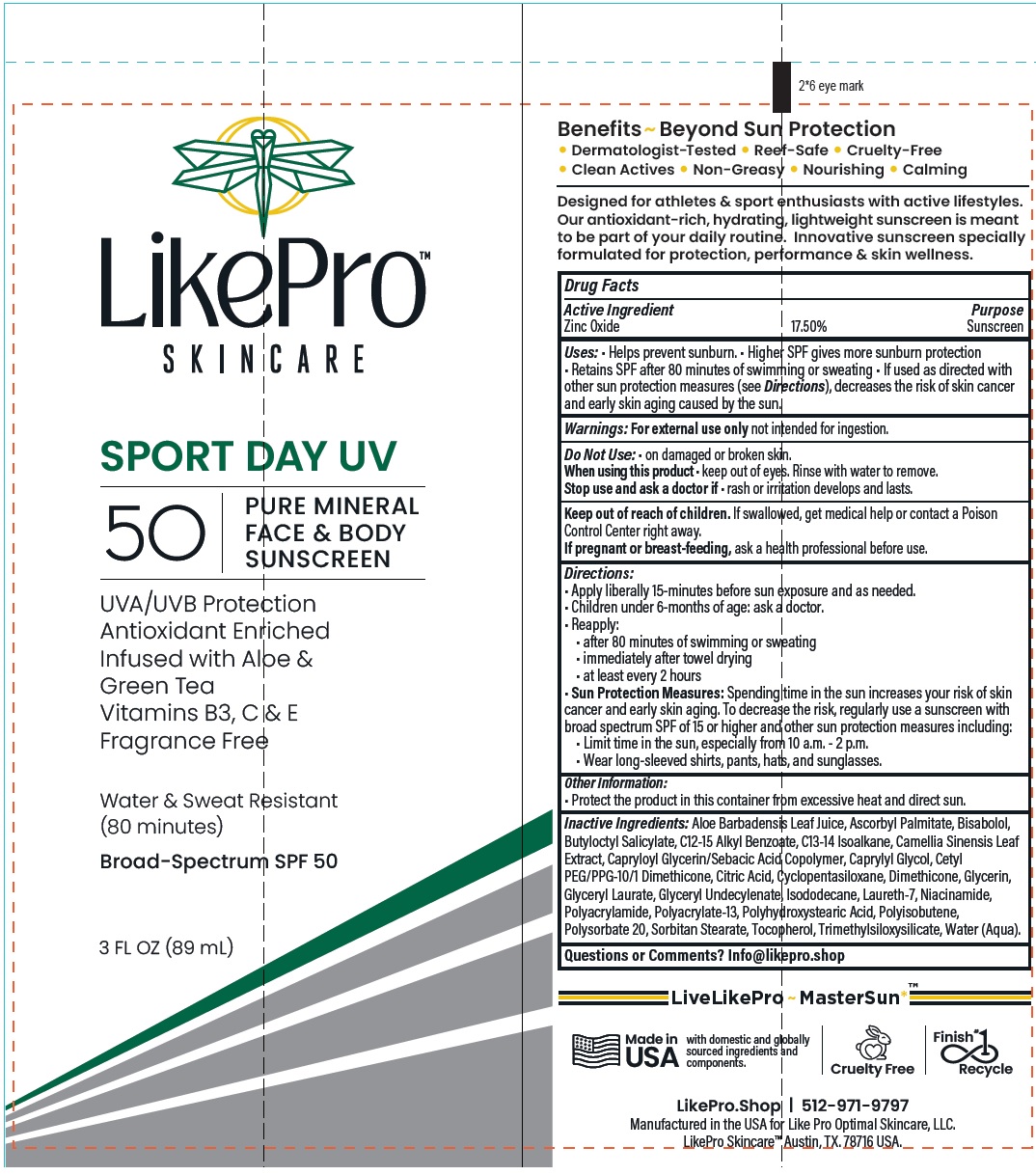 DRUG LABEL: LikePro Skincare Sport Day UV Face and Body Sunscreen SPF 50
NDC: 85750-611 | Form: CREAM
Manufacturer: LIKE PRO OPTIMAL SKINCARE LLC
Category: otc | Type: HUMAN OTC DRUG LABEL
Date: 20250603

ACTIVE INGREDIENTS: ZINC OXIDE 175 mg/1 mL
INACTIVE INGREDIENTS: ALOE VERA LEAF JUICE; ASCORBYL PALMITATE; BISABOLOL; BUTYLOCTYL SALICYLATE; ALKYL (C12-15) BENZOATE; C13-14 ISOPARAFFIN; GREEN TEA LEAF; CAPRYLYL GLYCOL; CITRIC ACID MONOHYDRATE; CYCLOPENTASILOXANE; DIMETHICONE; GLYCERIN; GLYCERYL LAURATE; ISODODECANE; LAURETH-7; NIACINAMIDE; POLYACRYLATE-13; POLYSORBATE 20; SORBITAN MONOSTEARATE; TOCOPHEROL; WATER

LikePro Skincare Sport Day UV Face and Body Sunscreen SPF 50

Active Ingredient

Zinc Oxide 17.50%

Purpose

Sunscreen

Uses:

- Helps prevent sunburn.
- Higher SPF gives more sunburn protection
- Retains SPF after 80 minutes of swimming or sweating
- If used as directed with other sun protection measures (see Directions), decreases the risk of skin cancer and early skin aging caused by the sun.

Warnings:

For external use only not intended for ingestion.

Do Not Use:

- on damaged or broken skin.

When using this product

- keep out of eyes. Rinse with water to remove.

Stop use and ask a doctor if

- rash or irritation develops and lasts.

Keep out of reach of children.

If swallowed, get medical help or contact a Poison Control Center right away.

If pregnant or breast-feeding,

ask a health professional before use.

Directions:

- Apply liberally 15-minutes before sun exposure and as needed.
- Children under 6-months of age: ask a doctor.
- Reapply:
- after 80 minutes of swimming or sweating
- immediately after towel drying
- at least every 2 hours
- Sun Protection Measures:Spending time in the sun increases your risk of skin cancer and early skin aging. To decrease the risk, regularly use a sunscreen with broad spectrum SPF of 15 or higher and other sun protection measures including:
- Limit time in the sun, especially from 10 a.m. - 2 p.m.
- Wear long-sleeved shirts, pants, hats, and sunglasses.

Other Information:

- Protect the product in this container from excessive heat and direct sun.

Inactive Ingredients:

Aloe Barbadensis Leaf Juice, Ascorbyl Palmitate, Bisabolol, Butyloctyl Salicylate, C12-15 Alkyl Benzoate, C13-14 Isoalkane, Camellia Sinensis Leaf Extract, Capryloyl Glycerin/Sebacic Acid Copolymer, Caprylyl Glycol, Cetyl PEG/PPG-10/1 Dimethicone, Citric Acid, Cyclopentasiloxane, Dimethicone, Glycerin, Glyceryl Laurate, Glyceryl Undecylenate, Isododecane, Laureth-7, Niacinamide, Polyacrylamide, Polyacrylate-13, Polyhydroxystearic Acid, Polyisobutene, Polysorbate 20, Sorbitan Stearate, Tocopherol, Trimethylsiloxysilicate, Water (Aqua).

Questions or Comments?

Info@likepro.shop